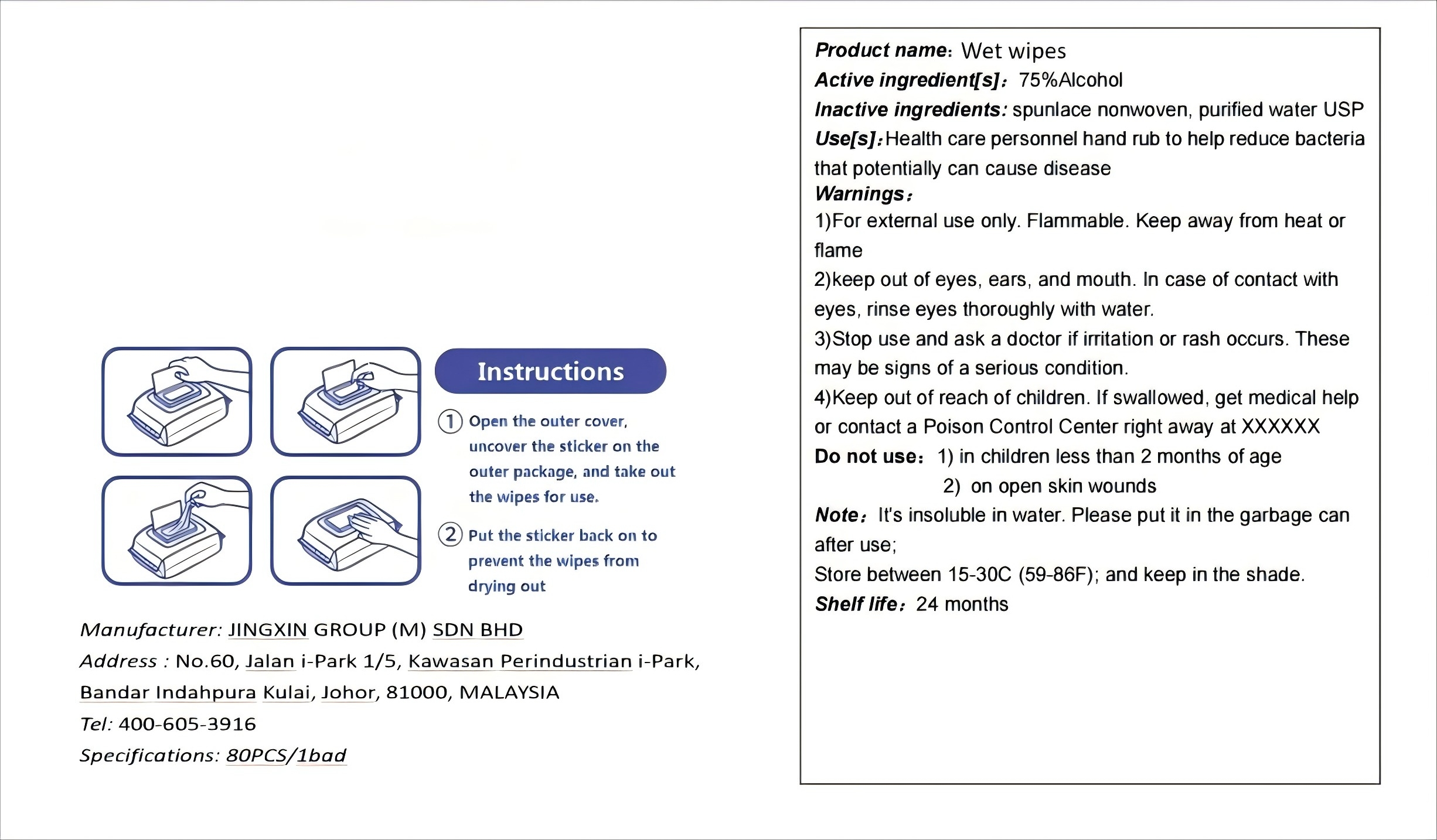 DRUG LABEL: Wet wipes
NDC: 85868-002 | Form: DRESSING
Manufacturer: JINGXIN GROUP (M) SDN BHD
Category: otc | Type: HUMAN OTC DRUG LABEL
Date: 20250707

ACTIVE INGREDIENTS: ALCOHOL 75 mL/100 mL
INACTIVE INGREDIENTS: WATER 25 mL/100 mL

ACTIVE INGREDIENT

Alcohol 75% v/v. Purpose: Antiseptic

PURPOSE

Hand Sanitizer to help reduce bacteria that potentially can cause disease. For use when soap and water are not available.

INDICATIONS AND USAGE

Hand Sanitizer to help reduce bacteria that potentially can cause disease. For use when soap and water are not available.

WARNINGS

For extemal use only. Flammable. Keep away from heat or flame.

DO NOT USE

in children less than 2 months of age.

on open skin wounds.

When using this product keep out of eyes,ears, and mouth. In case of contact with eyes, rinse eyes thoroughly with water.

Stop use and ask a doctor if irritation or rash occurs. Tese may be signs of a serious condition.

STORAGE AND HANDLING

Store between 15-30C (59-86F).

Avoid freezing and excessive heat above 40C (104F).

INACTIVE INGREDIENT

Cellulose and water.

DOSAGE AND ADMINISTRATION

Place enough product on hands to cover all surfaces.

Keep out of reach of children. If swallowed, get medical help or contact a Posion Control Center rihgt away.